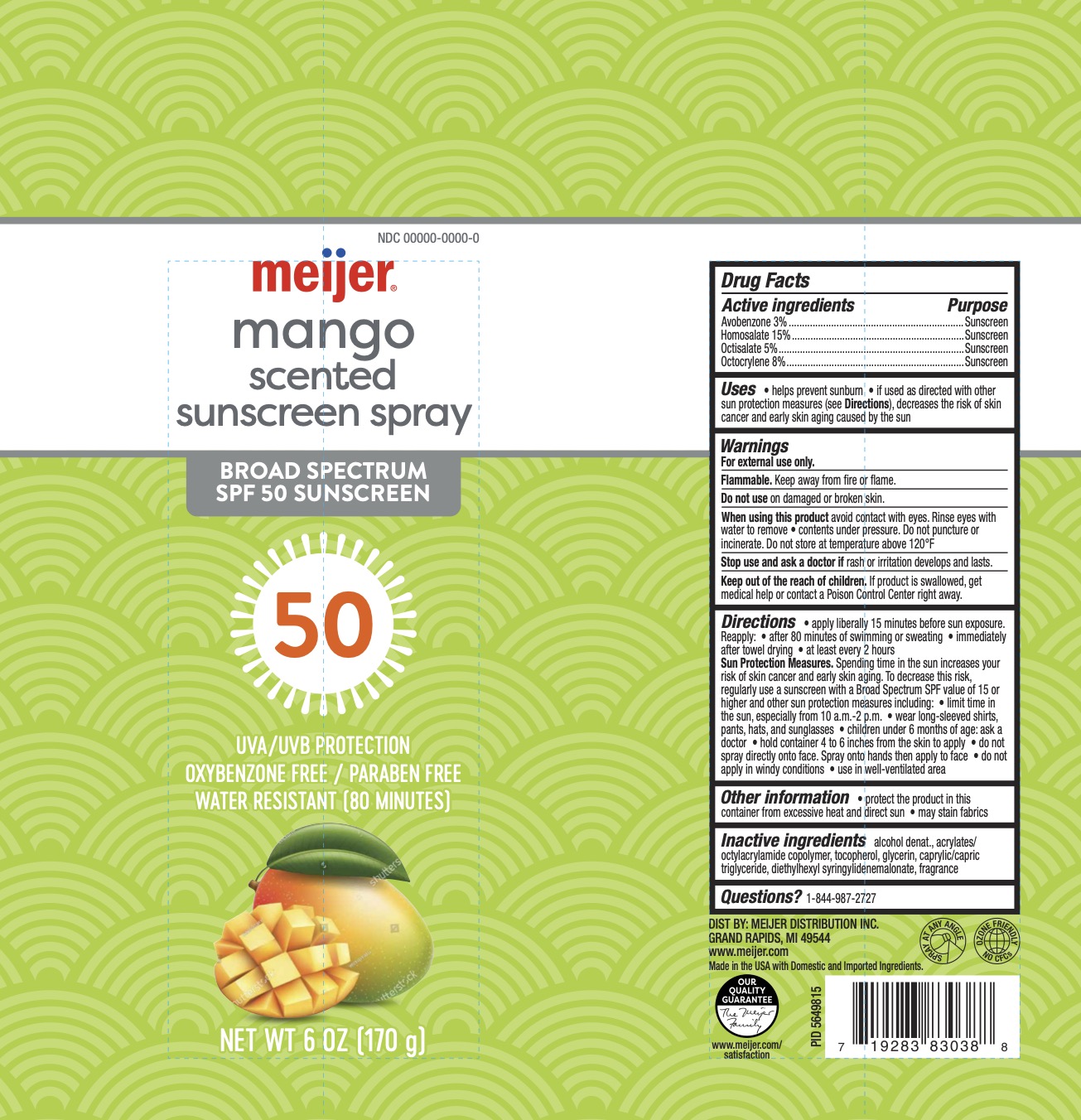 DRUG LABEL: Meijer SPF 50 Sunscreen Mango
NDC: 79481-1889 | Form: SPRAY
Manufacturer: Meijer
Category: otc | Type: HUMAN OTC DRUG LABEL
Date: 20251010

ACTIVE INGREDIENTS: OCTISALATE 5 g/100 g; HOMOSALATE 15 g/100 g; AVOBENZONE 3 g/100 g; OCTOCRYLENE 8 g/100 g
INACTIVE INGREDIENTS: MEDIUM-CHAIN TRIGLYCERIDES; ALCOHOL; TOCOPHEROL; DIETHYLHEXYL SYRINGYLIDENEMALONATE; ACRYLATES/OCTYLACRYLAMIDE COPOLYMER (40000 MW); GLYCERIN

Meijer SPF 50 Sunscreen CS Mango

ACTIVE INGREDIENT

Avobenzone 3%, Homosalate 15%, Octisalate 5%, Octocrylene 8%

PURPOSE

Sunscreen

INDICATIONS AND USAGE

Helps prevent sunburn.

If used as directed with other sun protection measures (see Directions), decreases the risk of skin cancer and early skin aging caused by the sun.

WARNINGS

For external use only.

Flammable. Do not use while smoking or near heat or flame.

Do not use on damaged or broken skin.

When using this product avoid contact with eyes. Rinse eyes with water to remove, contents under pressure. Do not puncture or incinerate. Do not store at temperature above 120F.

Stop use and ask a doctor if rash or irritation develops and lasts.

KEEP OUT OF REACH OF CHILDREN

If product is swallowed, get medical help or contact a Poison Control Center right away.

DOSAGE AND ADMINISTRATION

Apply liberally 15 minutes before sun exposure. Reapply: after 80 minutes of swimming or sweating, immediately after towel drying, at least every 2 hours.

Sun Protection Measures. Spending time in the sun increases your risk of skin cancer and early skin aging. To decrease this risk, regularly use a sunscreen with a Broad Spectrum SPF value of 15 or higher and other sun protection measures including: limit time in the sun, especially from 10 a.m. - 2 p.m., wear long-sleeved shirts, pants, hats, and sunglasses, children under 6 months of age: ask a doctor, hold container 4 to 6 inches from the skin to apply, do not spray directly onto face Spray onto hand then apply to face, do not apply in windy conditions, use in well-ventilated area.

INACTIVE INGREDIENT

Alcohol denat., acrylates/octylacrylamide copolymer, tocopherol, glycerin, caprylic/capric triglyceride, diethylhexyl syringylidenemalonate, fragrance.